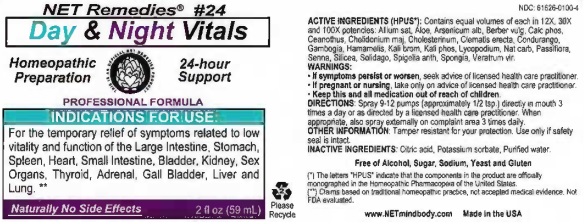 DRUG LABEL: Day and Night Vitals
NDC: 61626-0100 | Form: LIQUID
Manufacturer: NET Remedies
Category: homeopathic | Type: HUMAN PRESCRIPTION DRUG LABEL
Date: 20210119

ACTIVE INGREDIENTS: GARLIC 12 [hp_X]/59 mL; ALOE VERA LEAF 12 [hp_X]/59 mL; ARSENIC TRIOXIDE 12 [hp_X]/59 mL; BERBERIS VULGARIS ROOT BARK 12 [hp_X]/59 mL; TRIBASIC CALCIUM PHOSPHATE 12 [hp_X]/59 mL; CEANOTHUS AMERICANUS LEAF 12 [hp_X]/59 mL; CHELIDONIUM MAJUS 12 [hp_X]/59 mL; CHOLESTEROL 12 [hp_X]/59 mL; CLEMATIS RECTA FLOWERING TOP 12 [hp_X]/59 mL; MARSDENIA CONDURANGO BARK 12 [hp_X]/59 mL; GAMBOGE 12 [hp_X]/59 mL; HAMAMELIS VIRGINIANA ROOT BARK/STEM BARK 12 [hp_X]/59 mL; POTASSIUM BROMIDE 12 [hp_X]/59 mL; DIBASIC POTASSIUM PHOSPHATE 12 [hp_X]/59 mL; LYCOPODIUM CLAVATUM SPORE 12 [hp_X]/59 mL; SODIUM CARBONATE 12 [hp_X]/59 mL; PASSIFLORA INCARNATA TOP 12 [hp_X]/59 mL; SENNA LEAF 12 [hp_X]/59 mL; SILICON DIOXIDE 12 [hp_X]/59 mL; SOLIDAGO VIRGAUREA FLOWERING TOP 12 [hp_X]/59 mL; SPIGELIA ANTHELMIA 12 [hp_X]/59 mL; SPONGIA OFFICINALIS SKELETON, ROASTED 12 [hp_X]/59 mL; VERATRUM VIRIDE ROOT 12 [hp_X]/59 mL
INACTIVE INGREDIENTS: CITRIC ACID MONOHYDRATE; POTASSIUM SORBATE; WATER

Day and Night Vitals

ACTIVE INGREDIENT

ACTIVE INGREDIENTS (HPUS*): Contains equal amounts of each in 12X, 30X and 100X potencies: Allium sat, Aloe, Arsenicum alb, Berber vulg, Calc phos, Ceanothus, Chelidonium maj, Cholesterinum, Clematic erecta, Condurango, Gambogia, Hamamelis, Kali brom, Kali phos, Lycopodium, Nat carb, Passiflora, Senna, Silicea, Solidago, Spigelia anth, Spongia, Veratrum vir.

(*) The letters "HPUS" indicate that the components in the product are officially monographed in the Homeopathic Pharmacopeia of the United States.

(**) Claims based on traditional homeopathic practice, not accepted medical evidence. Not FDA evaluated.

INDICATIONS AND USAGE

INDICATIONS FOR USE: For the temporary relief of symptoms related to low vitality and function of the Large intestine, Stomach, Spleen, Heart, Small Intestine, Bladder, Kidney, Sex Organs, Thyroid, Adrenal, Gall Bladder, Liver and Lung.**

WARNINGS:

• If symptoms persist or worsen, seek advice of licensed health care practitioner.

• If pregnant or nursing, take only on advice of licensed health care practitioner.

• Keep this and all medication out of reach of children.

KEEP OUT OF REACH OF CHILDREN

• Keep this and all medication out of reach of children.

DOSAGE AND ADMINISTRATION

DIRECTIONS: Spray 9-12 pumps (approximately 1/2 tsp.) directly in mouth 3 times a day or as directed by a licensed health care practitioner. When appropriate, also spray externally on complaint area 3 times daily.

OTHER INFORMATION: Tamper resistant for your protection. Use only if safetly seal is intact.

INACTIVE INGREDIENTS: Citrid acid, Potassium sorbate, Purified water.

Free of Alcohol, Sodium, Yeast and Gluten.

QUESTIONS

www.NETmindbody.com

Made in the USA.

PACKAGE LABEL

NET Remedies #24

Homeopathic Preparation

24-hour Support

PROFESSIONAL FORMULA

Naturally No Side Effects 2 fl oz (59 mL)

PURPOSE

INDICATIONS FOR USE: For the temporary relief of symptoms related to low vitality and function of the Large intestine, Stomach, Spleen, Heart, Small Intestine, Bladder, Kidney, Sex Organs, Thyroid, Adrenal, Gall Bladder, Liver and Lung.**